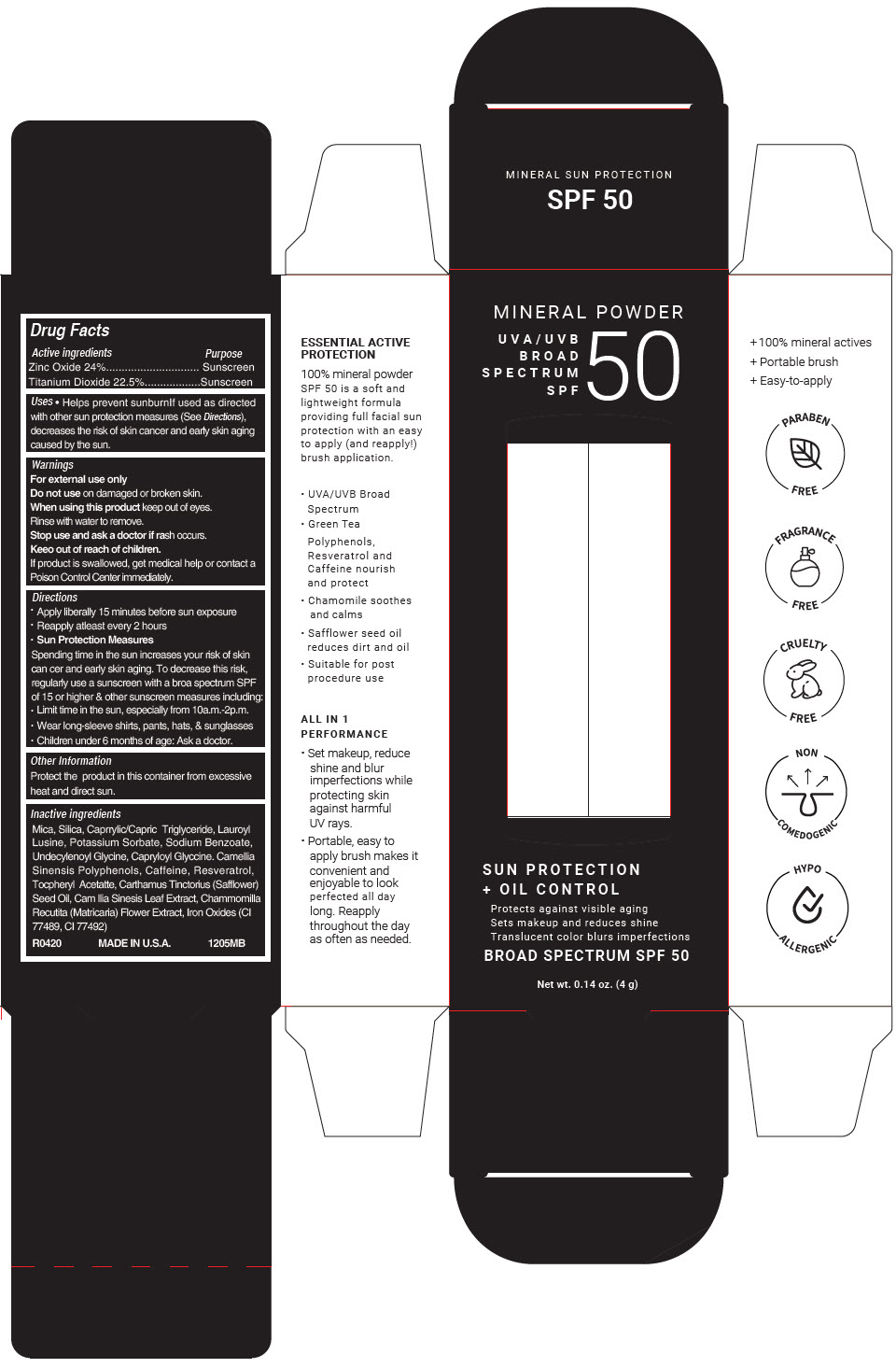 DRUG LABEL: Mineral Sunscreen
NDC: 51326-125 | Form: POWDER
Manufacturer: Topiderm, Inc.
Category: otc | Type: HUMAN OTC DRUG LABEL
Date: 20230213

ACTIVE INGREDIENTS: ZINC OXIDE 240 mg/1 g; TITANIUM DIOXIDE 225 mg/1 g
INACTIVE INGREDIENTS: MICA; SILICON DIOXIDE; MEDIUM-CHAIN TRIGLYCERIDES; LAUROYL LYSINE; POTASSIUM SORBATE; SODIUM BENZOATE; GREEN TEA LEAF; CAFFEINE; RESVERATROL; .ALPHA.-TOCOPHEROL; SAFFLOWER OIL; CHAMOMILE

Mineral Sunscreen
SPF 50

Drug Facts

ACTIVE INGREDIENT

Active ingredients | Purpose
Zinc Oxide 24% | Sunscreen
Titanium Dioxide 22.5% | Sunscreen

Uses

- Helps prevent sunburnIf used as directed with other sun protection measures (See Directions), decreases the risk of skin cancer and early skin aging caused by the sun.

Warnings

For external use only

Do not use on damaged or broken skin.

When using this product keep out of eyes.

Rinse with water to remove.

Stop use and ask a doctor if rash occurs.

Keeo out of reach of children.

If product is swallowed, get medical help or contact a Poison Control Center immediately.

Directions

- Apply liberally 15 minutes before sun exposure
- Reapply atleast every 2 hours
- Sun Protection Measures

Spending time in the sun increases your risk of skin can cer and early skin aging. To decrease this risk, regularly use a sunscreen with a broa spectrum SPF of 15 or higher & other sunscreen measures including:

- Limit time in the sun, especially from 10a.m.-2p.m.
- Wear long-sleeve shirts, pants, hats, & sunglasses
- Children under 6 months of age: Ask a doctor.

Other Information

Protect the product in this container from excessive heat and direct sun.

Inactive ingredients

Mica, Silica, Caprrylic/Capric Triglyceride, Lauroyl Lusine, Potassium Sorbate, Sodium Benzoate, Undecylenoyl Glycine, Capryloyl Glyccine. Camellia Sinensis Polyphenols, Caffeine, Resveratrol, Tocpheryl Acetatte, Carthamus Tinctorius (Safflower) Seed Oil, Cam llia Sinesis Leaf Extract, Chammomilla Recutita (Matricaria) Flower Extract, Iron Oxides (CI 77489, CI 77492)

PRINCIPAL DISPLAY PANEL - 4 g Tube Carton

MINERAL POWDER
UVA/UVB
BROAD
SPECTRUM
SPF
50

SUN PROTECTION
+ OIL CONTROL

Protects against visible aging
Sets makeup and reduces shine
Translucent color blurs imperfections

BROAD SPECTRUM SPF 50

Net wt. 0.14 oz. (4 g)